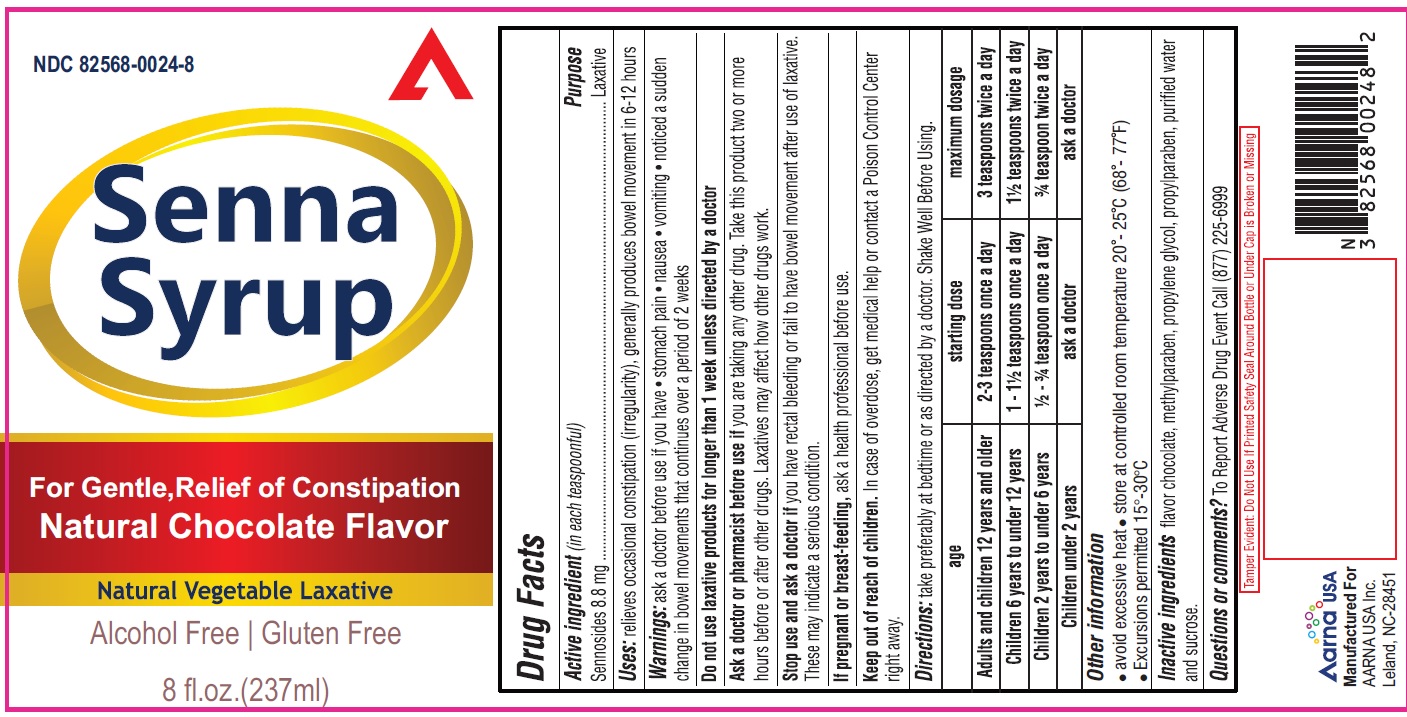 DRUG LABEL: Senna
NDC: 82568-0024 | Form: SYRUP
Manufacturer: AARNA USA INC.
Category: otc | Type: HUMAN OTC DRUG LABEL
Date: 20250320

ACTIVE INGREDIENTS: SENNOSIDES 8.8 mg/5 mL
INACTIVE INGREDIENTS: METHYLPARABEN; PROPYLENE GLYCOL; PROPYLPARABEN; WATER; SUCROSE

Senna Syrup
Natural Choclate Flavor
Natural Vegitable Lexative
Alcohol Free and Gluten Free

Drug Facts

Active ingredient (in each teaspoonful)

Sennosides 8.8 mg

Purpose

Laxative

Uses

- relieves occasional constipation (irregularity)
- generally causes a bowel movement in 6-12 hours

WARNINGS

Do not use

laxative products for longer than one week unless directed by a doctor

Ask a doctor or pharmacist belore use

if you are taking any other drug. Take this product two or more hours belore or after other drugs. Laxatives may affect how other drugs work

Stop use and ask a doctor if

you have rectal bleeding or fail to have bowel movement after use of laxative. These may indicate a serious condition.

If pregnant or breast-feeding,

ask a health care professional before use.

OVERDOSAGE

In case of overdose, get medical help or contact a Poison Control Center right away.

Directions

take preferably at bedtime or as directed by a doctor. Shake Well Before Using.

age | starting dosage | maximum dosage
Adults and children; 12 years and older | 2-3 teaspoons once a day | 3 teaspoons twice a day
Children 6 years to under; 12 years | 1-1½ teaspoons once a day | 1½ teaspoons twice a day
Children 2 years to under; 6 years | ½ - ¾ teaspoon once a day | ¾ teaspoon twice a day
Children under; 2 years | ask a doctor | ask a doctor

Other information

- avoid excessive heat ! store at controlled room temperature 20 - 25 C (68 - 77 F)
- Excursions permitted 15°-30°C

Inactive ingredients

flavor chocolate, methylparaben, propylene glycol, propylparaben, purified water and sucrose.

Questions or comments?

To Report Adverse Drug Event Call (877) 225·6999

Manufactured for:

AARNA USA INC.

Leland, NC-28451